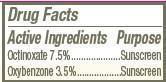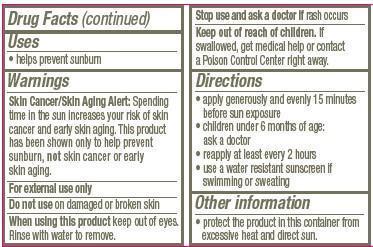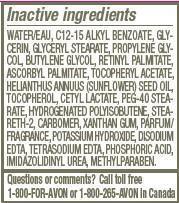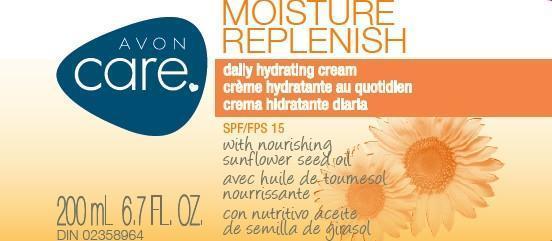 DRUG LABEL: Avon Care
NDC: 10096-0262 | Form: CREAM
Manufacturer: Avon Products, Inc.
Category: otc | Type: HUMAN OTC DRUG LABEL
Date: 20130212

ACTIVE INGREDIENTS: OCTINOXATE 75 mg/1 mL; OXYBENZONE 35 mg/1 mL

Active Ingredients
Octinoxate 7.5%...................
Oxybenzone 3.5%................

Purpose
...........Sunscreen
.........Sunscreen

Uses
• helps prevent sunburn

Warnings
Skin Cancer/Skin Aging Alert: Spending time in the sun increases your risk of skin cancer and early skin aging. This product has been shown only to help prevent sunburn, not skin cancer or early skin aging.
For external use only

Do not use on damaged or broken skin

When using this product keep out of eyes. Rinse with water to remove.

Stop use and ask a doctor if rash occurs

Keep out of reach of children. If swallowed, get medical help or contact a Poison Control Center right away.

Directions
• apply generously and evenly 15 minutes before sun exposure
• children under 6 months of age: ask a doctor
• reapply at least every 2 hours
• use a water resistant sunscreen if swimming or sweating

Other information
• protect the product in this container from excessive heat and direct sun.

Inactive ingredients
WATER/EAU, C12-15 ALKYL BENZOATE, GLYCERIN, GLYCERYL STEARATE, PROPYLENE GLYCOL, BUTYLENE GLYCOL, RETINYL PALMITATE, ASCORBYL PALMITATE, TOCOPHERYL ACETATE, HELIANTHUS ANNUUS (SUNFLOWER) SEED OIL, TOCOPHEROL, CETYL LACTATE, PEG-40 STEARATE, HYDROGENATED POLYISOBUTENE, STEARETH-2, CARBOMER, XANTHAN GUM, PARFUM/FRAGRANCE, POTASSIUM HYDROXIDE, DISODIUM EDTA, TETRASODIUM EDTA, PHOSPHORIC ACID, IMIDAZOLIDINYL UREA, METHYLPARABEN.

Questions or comments? Call toll free 1-800-FOR-AVON or 1-800-265-AVON in Canada